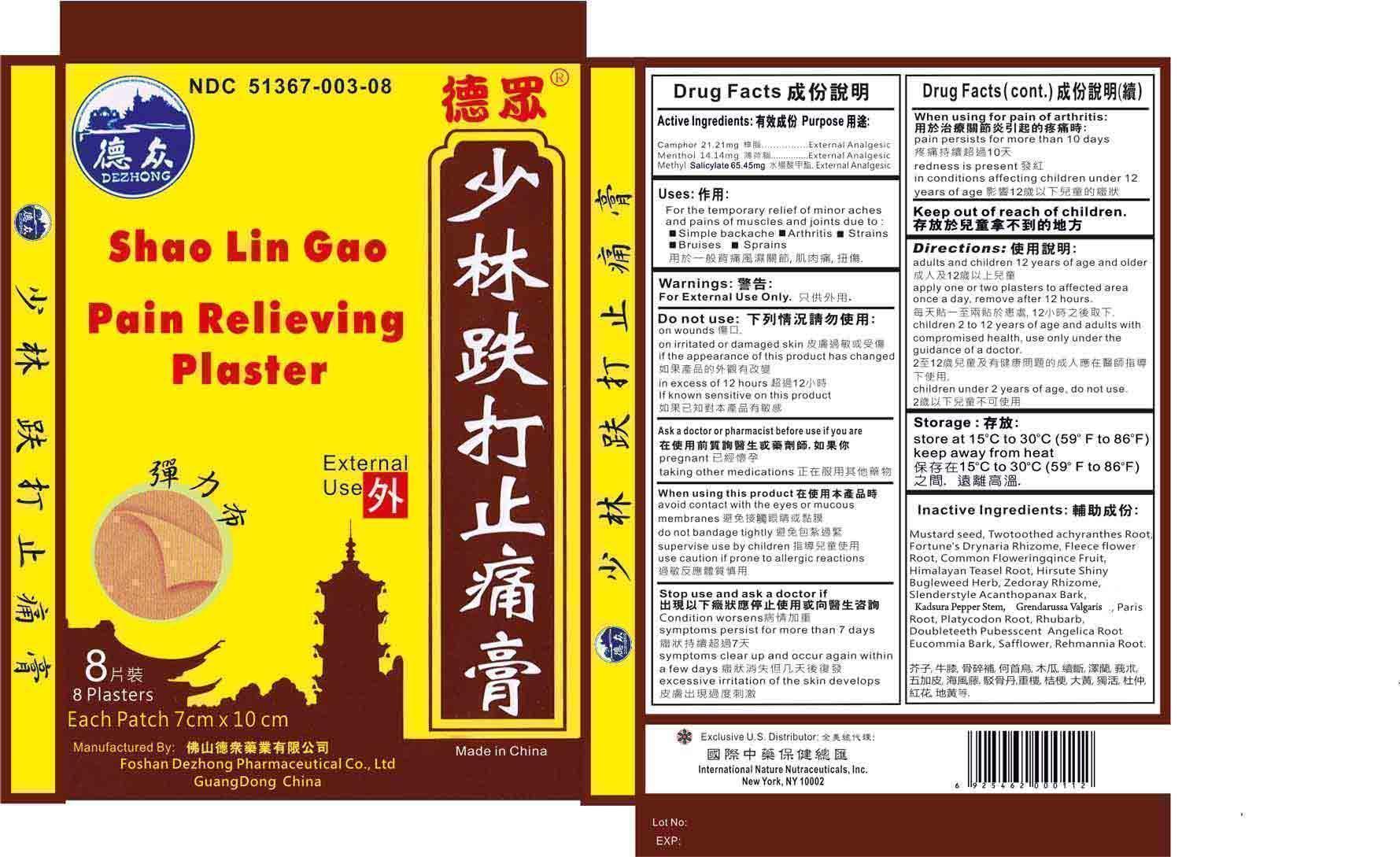 DRUG LABEL: Shao Lin Gao Pain Relieving Plaster
NDC: 51367-003 | Form: PLASTER
Manufacturer: International Nature Nutraceuticals
Category: otc | Type: HUMAN OTC DRUG LABEL
Date: 20120801

ACTIVE INGREDIENTS: CAMPHOR (NATURAL) 21.21 mg/1 1; MENTHOL 14.14 mg/1 1; METHYL SALICYLATE 64.45 mg/1 1
INACTIVE INGREDIENTS: MUSTARD SEED; ACHYRANTHES BIDENTATA ROOT; DRYNARIA FORTUNEI ROOT; FALLOPIA MULTIFLORA ROOT; CHAENOMELES SINENSIS FRUIT; DIPSACUS ASPER ROOT; EUPATORIUM JAPONICUM WHOLE; ZEDOARY; ELEUTHEROCOCCUS NODIFLORUS ROOT BARK; PIPER KADSURA STEM; JUSTICIA GENDARUSSA LEAF; PARIS POLYPHYLLA ROOT; PLATYCODON GRANDIFLORUM ROOT; RHUBARB; ANGELICA PUBESCENS ROOT; EUCOMMIA ULMOIDES BARK; SAFFLOWER; REHMANNIA GLUTINOSA ROOT

Drug Facts

Active Ingredients

Camphor- 21.21 mg

Menthol- 14.14 mg

Methyl Salicylate- 65.45 mg

Uses

For the temporary relief of minor aches and pains of muscles or joints due to:

- Simple backache
- Arthritis
- Sprains
- Bruises
- Strains

Warnings

For external use only

Do Not Use

On wounds

On irritated or damaged skin

If the color of the product has changed

In excess of 12 hours

If known sensitive to the product

Ask a doctor or a pharmacist before use if you are

Pregnant

Taking other medications

When Using This Product

Avoid contact with eyes and mucous membranes

Do not bandage tightly

Supervise child use

Use caution if prone to allergic reactions

Stop use and ask doctor if

Condition worsens

Symptoms persist for more than 7 days

Symptoms clear up and occur again within a few days

Excessive irritation of the skin develops

When Using for Pain of Arthritis: Stop Use If

Pain persists for more than 10 days

Redness is present

In conditions affecting children under 12 years of age

Directions

Adults and children 12 years of age and older- apply one or two plasters to affected area once a day, remove after 12 hours

Children 2 to 12 years and adults with compromised health- use only under the guidance of a doctor

Children under 2 years of age- do not use

Storage

Store at 15°C to 30°C (59°F to 86°F)

Keep Away From Heat

Inactive Ingredients

Mustard Seed, Twotoothed Achranthes Root, Fortune's Drynaria Rhizome, Fleeceflower Root, Common Floweringqince Fruit, Himalayan Teasel Root, Hirsute Shiny Bugleweed Herb, Zedoary Rhizome, Slenderstyle Acanthopanax Bark, Thickleaf Croton Root, Root of Fruitcose Brevnia, Paris Root, Platycodon, Rhubarb, Doubleteeth Pubesscent Angelica Root, Eucommia Bark, Safflower, Rehmannia Root